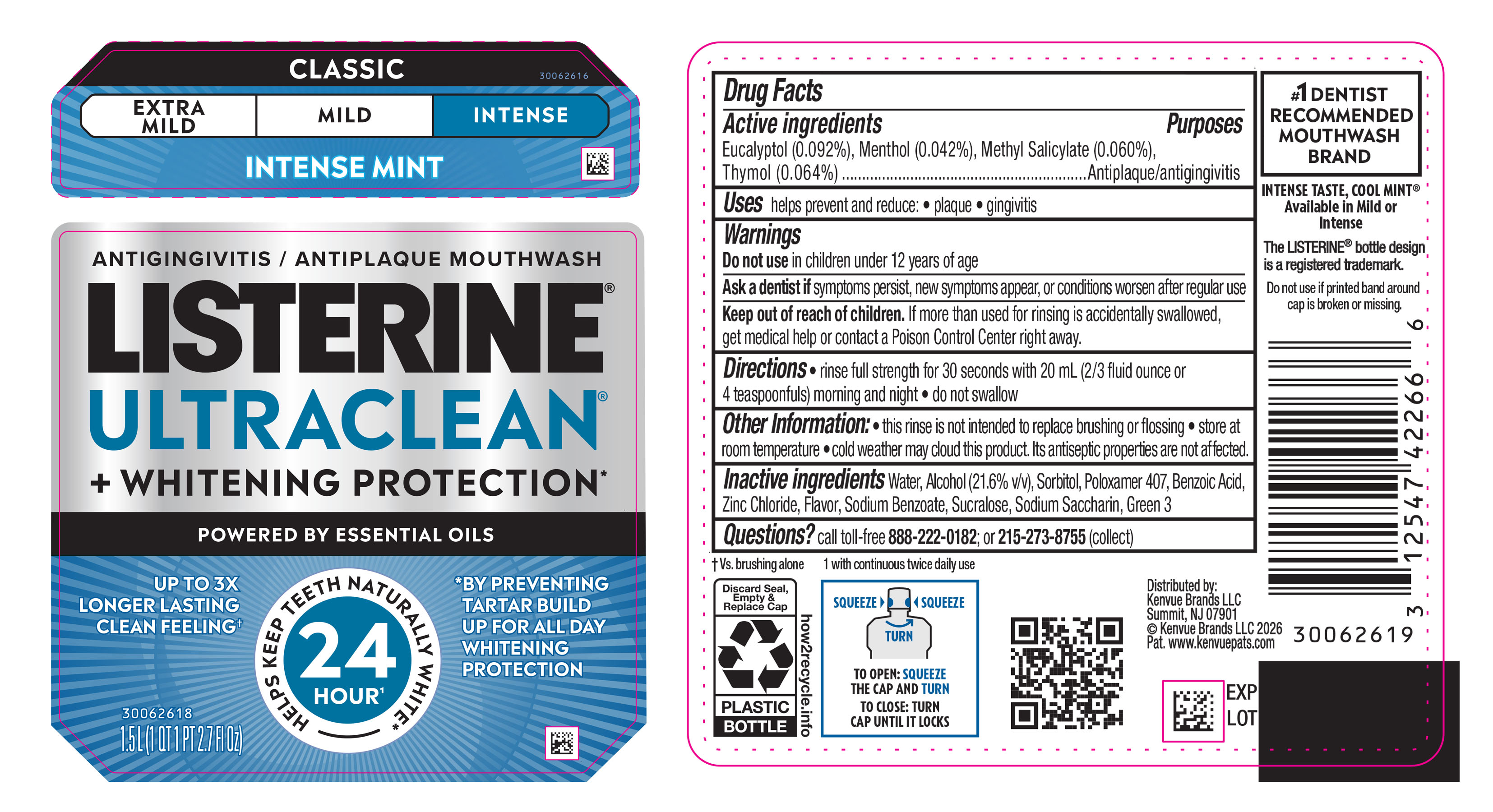 DRUG LABEL: Listerine UltraClean Plus Whitening Protection Intense Antiseptic Antigingivitis/ Antiplaque Mouthwash
NDC: 69968-0959 | Form: MOUTHWASH
Manufacturer: Kenvue Brands LLC
Category: otc | Type: HUMAN OTC DRUG LABEL
Date: 20260202

ACTIVE INGREDIENTS: METHYL SALICYLATE 0.6 mg/1 mL; THYMOL 0.64 mg/1 mL; EUCALYPTOL 0.92 mg/1 mL; MENTHOL 0.42 mg/1 mL
INACTIVE INGREDIENTS: WATER; ALCOHOL; POLOXAMER 407; BENZOIC ACID; SODIUM BENZOATE; SORBITOL; SUCRALOSE; GREEN 3; ZINC CHLORIDE; SODIUM SACCHARIN

Listerine UltraClean + Whitening Protection Intense Antiseptic Antigingivitis/ Antiplaque Mouthwash

Drug Facts

Active ingredients

Eucalyptol (0.092%)

Menthol (0.042%)

Methyl Salicylate (0.060%)

Thymol (0.064%)

Purposes

Antiplaque/antigingivitis

Uses

helps prevent and reduce: • plaque • gingivitis

Warnings

Do not use in children under 12 years of age

Ask a dentist if symptoms persist, new symptoms appear, or conditions worsen after regular use

Keep out of reach of children. If more than used for rinsing is accidentally swallowed, get medical help or contact a Poison Control Center right away.

Directions

• rinse full strength for 30 seconds with 20 mL (2/3 fluid ounce or 4 teaspoonfuls) morning and night

• do not swallow

Other information

- this rinse is not intended to replace brushing or flossing
- store at room temperature
- cold weather may cloud this product. Its antiseptic properties are not affected.

Inactive ingredients

Water, Alcohol (21.6% v/v), Sorbitol, Poloxamer 407, Benzoic Acid, Zinc Chloride, Flavor, Sodium Benzoate, Sucralose, Sodium Saccharin, Green 3

Questions?

call toll-free 888-222-0182 or 215-273-8755 (collect)

Distributed by:
Kenvue Brands LLC
Summit, NJ 07901

PRINCIPAL DISPLAY PANEL - 1.5 L Bottle Label

ANTIGINGIVITIS / ANTIPLAQUE MOUTHWASH

LISTERINE®

ULTRACLEAN®

+ WHITENING PROTECTION*

POWERED BY ESSENTIAL OILS

UP TO 3X

LONGER LASTING

CLEAN FEELING†

24

HOUR^1

HELPS KEEP TEETH NATURALLY WHITE*

*BY PREVENTING

TARTAR BUILD

UP FOR ALL DAY

WHITENING

PROTECTION

1.5 L (1 QT 1 PT 2.7 FL Oz)